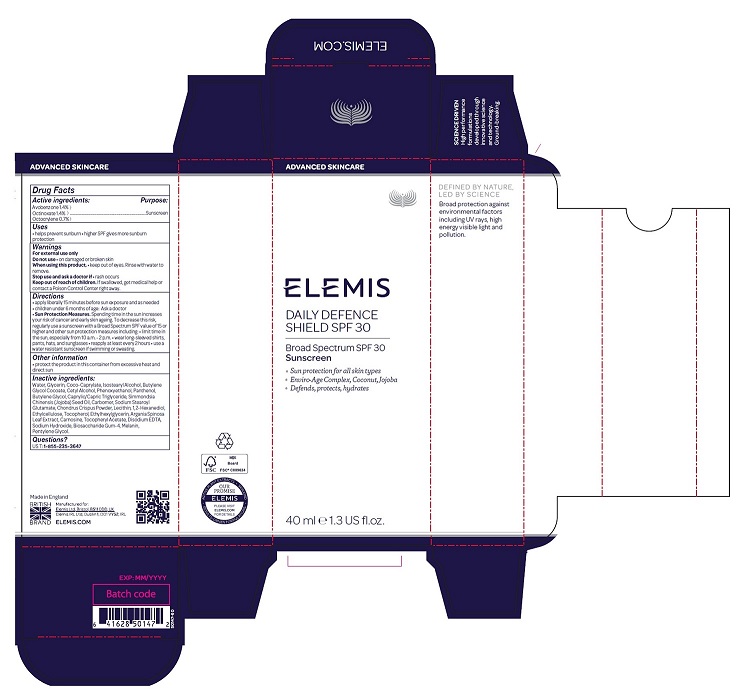 DRUG LABEL: Daily Defence Shield
NDC: 65912-003 | Form: CREAM
Manufacturer: ELEMIS Limited
Category: otc | Type: HUMAN OTC DRUG LABEL
Date: 20251119

ACTIVE INGREDIENTS: AVOBENZONE 14 mg/1 g; OCTINOXATE 14 mg/1 g; OCTOCRYLENE 7 mg/1 g
INACTIVE INGREDIENTS: GLYCERIN; COCO-CAPRYLATE; WATER; ISOSTEARYL ALCOHOL; CETYL ALCOHOL; PHENOXYETHANOL; PANTHENOL; BUTYLENE GLYCOL; JOJOBA OIL; SODIUM STEAROYL GLUTAMATE; CHONDRUS CRISPUS; LECITHIN, SOYBEAN; 1,2-HEXANEDIOL; ETHYLCELLULOSE, UNSPECIFIED; TOCOPHEROL; ETHYLHEXYLGLYCERIN; ARGANIA SPINOSA LEAF; CARNOSINE; .ALPHA.-TOCOPHEROL ACETATE; EDETATE DISODIUM ANHYDROUS; SODIUM HYDROXIDE; BIOSACCHARIDE GUM-4; MELANIN SYNTHETIC (TYROSINE, PEROXIDE); PENTYLENE GLYCOL; MEDIUM-CHAIN TRIGLYCERIDES

Daily Defence Shield
SPF 30

Drug Facts

Active ingredients

Avobenzone 1.4% }
Octinoxate 1.4% }
Octocrylene 0.7%}

Purpose

Sunscreen

Uses

- helps prevent sunburn
- higher SPF gives more sunburn protection

Warnings

For external use only

Do not use

- on damaged or broken skin

When using this product

- keep out of eyes. Rinse with water to remove.

Stop use and ask a doctor if

- rash occurs

Keep out of reach of children. If swallowed, get medical help or contact a Poison Control Center right away.

Directions

- apply liberally and evenly 15 minutes before sun exposure and as needed
- children under 6 months of age: Ask a doctor
- Sun Protection Measures. Spending time in the sun increases your risk of skin cancer and early skin ageing. To decrease this risk, regularly use a sunscreen with a Broad Spectrum SPF value of 15 or higher and other sun protection measures including:
  - limit time in the sun, especially from 10 a.m. - 2 p.m.
  - wear long-sleeved shirts, pants, hats, and sunglasses
  - reapply at least every 2 hours
  - use a water resistant sunscreen if swimming or sweating

Other information

- protect the product in this container from excessive heat and direct sun

Inactive ingredients

Water, Glycerin, Coco-Caprylate, Isostearyl Alcohol, Butylene Glycol Cocoate, Cetyl Alcohol, Phenoxyethanol, Panthenol, Butylene Glycol, Cocos Nucifera (Coconut) Oil, Simmondsia Chinensis (Jojoba) Seed Oil, Carbomer, Sodium Stearoyl Glutamate, Chondrus Crispus Powder, Lecithin, 1,2-Hexanediol, Ethylcellulose, Tocopherol, Ethylhexylglycerin, Argania Spinosa Leaf Extract, Carnosine, Tocopheryl Acetate, Disodium EDTA, Sodium Hydroxide, Biosaccharide Gum-4, Melanin, Pentylene Glycol.

Questions?

US T: 1-855-235-3647

PRINCIPAL DISPLAY PANEL - 40 ml Tube Carton

ADVANCED SKINCARE

ELEMIS

DAILY DEFENCE
SHIELD SPF 30

Broad Spectrum SPF 30
Sunscreen

- Sun protection for all skin types
- Enviro-Age Complex, Coconut,
  Jojoba
- Defends, protects, hydrates

40 ml e 1.3 US fl.oz.